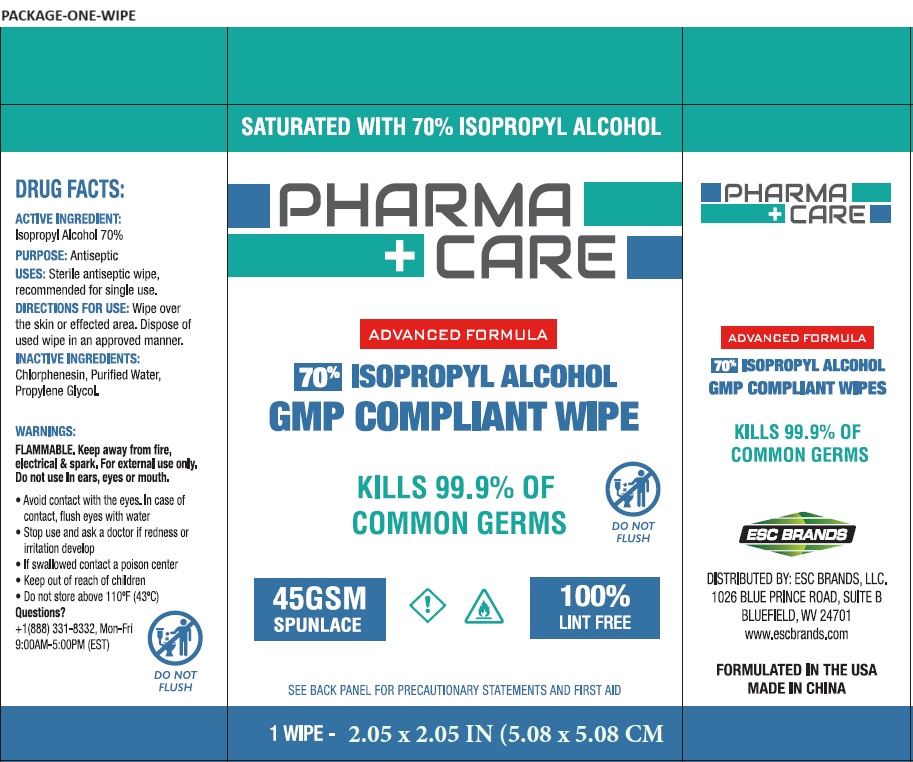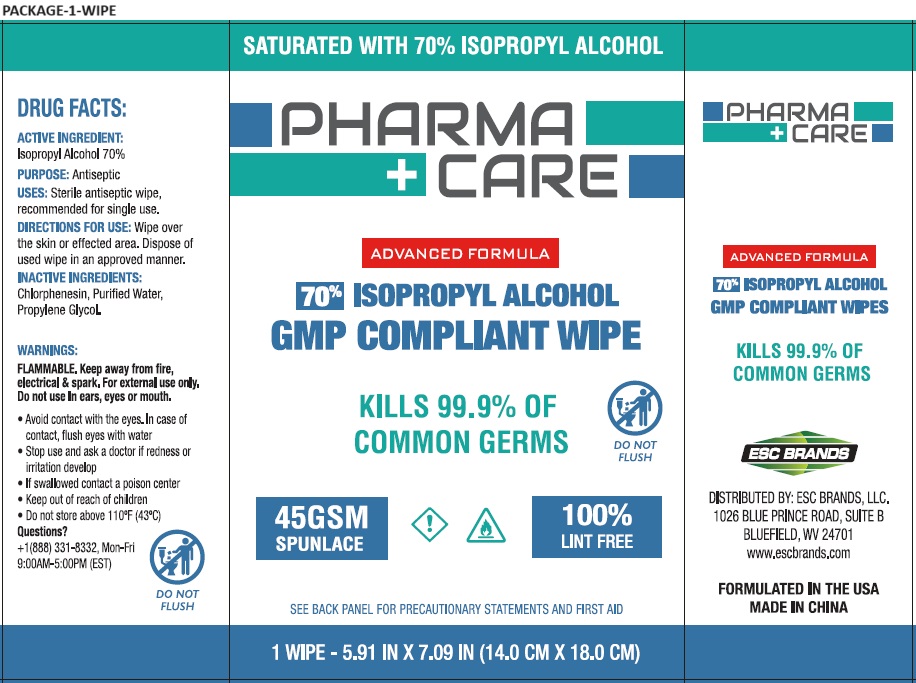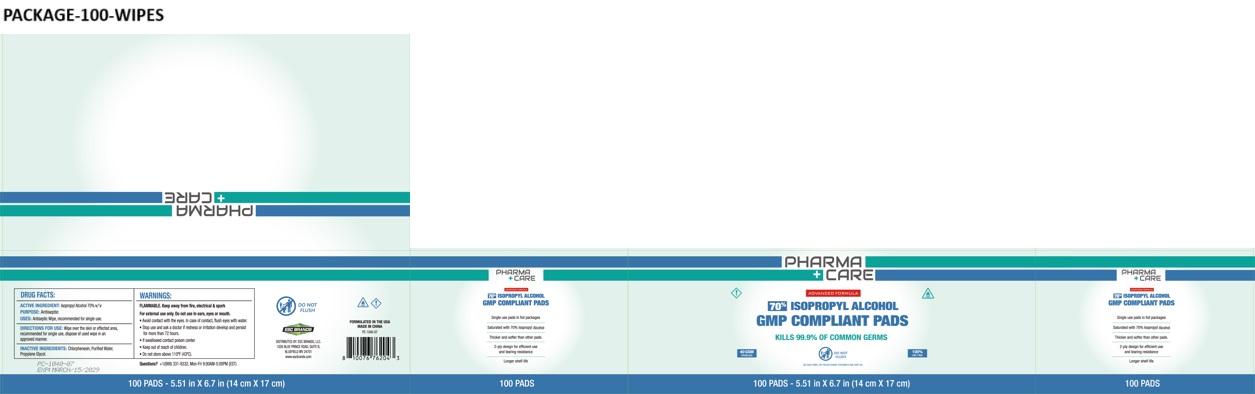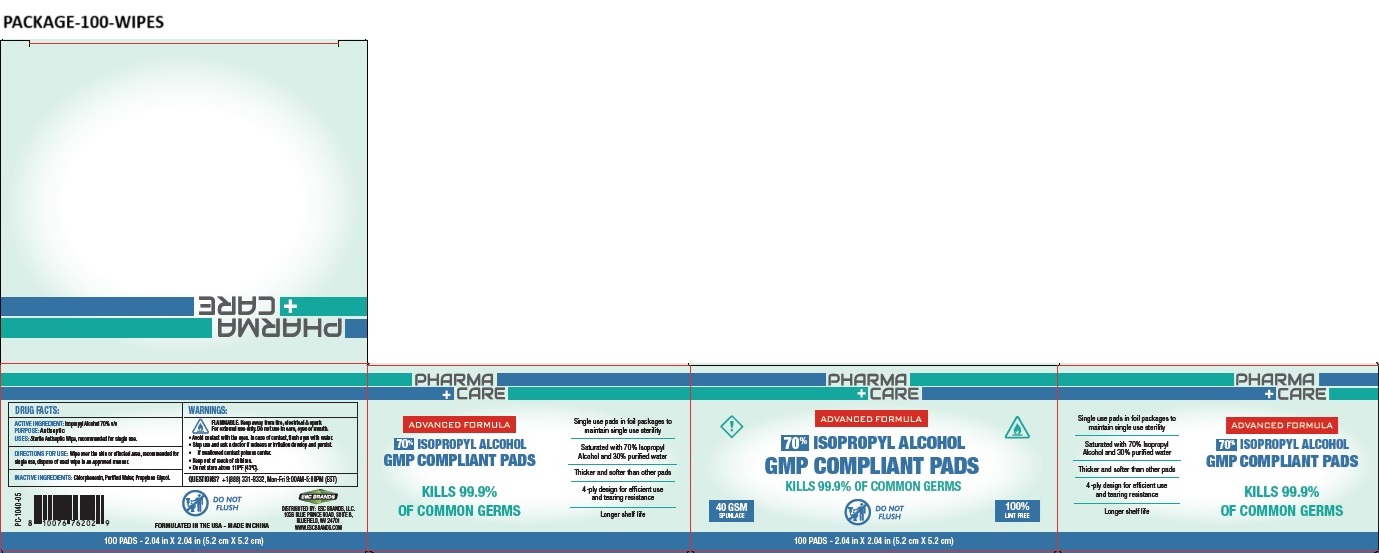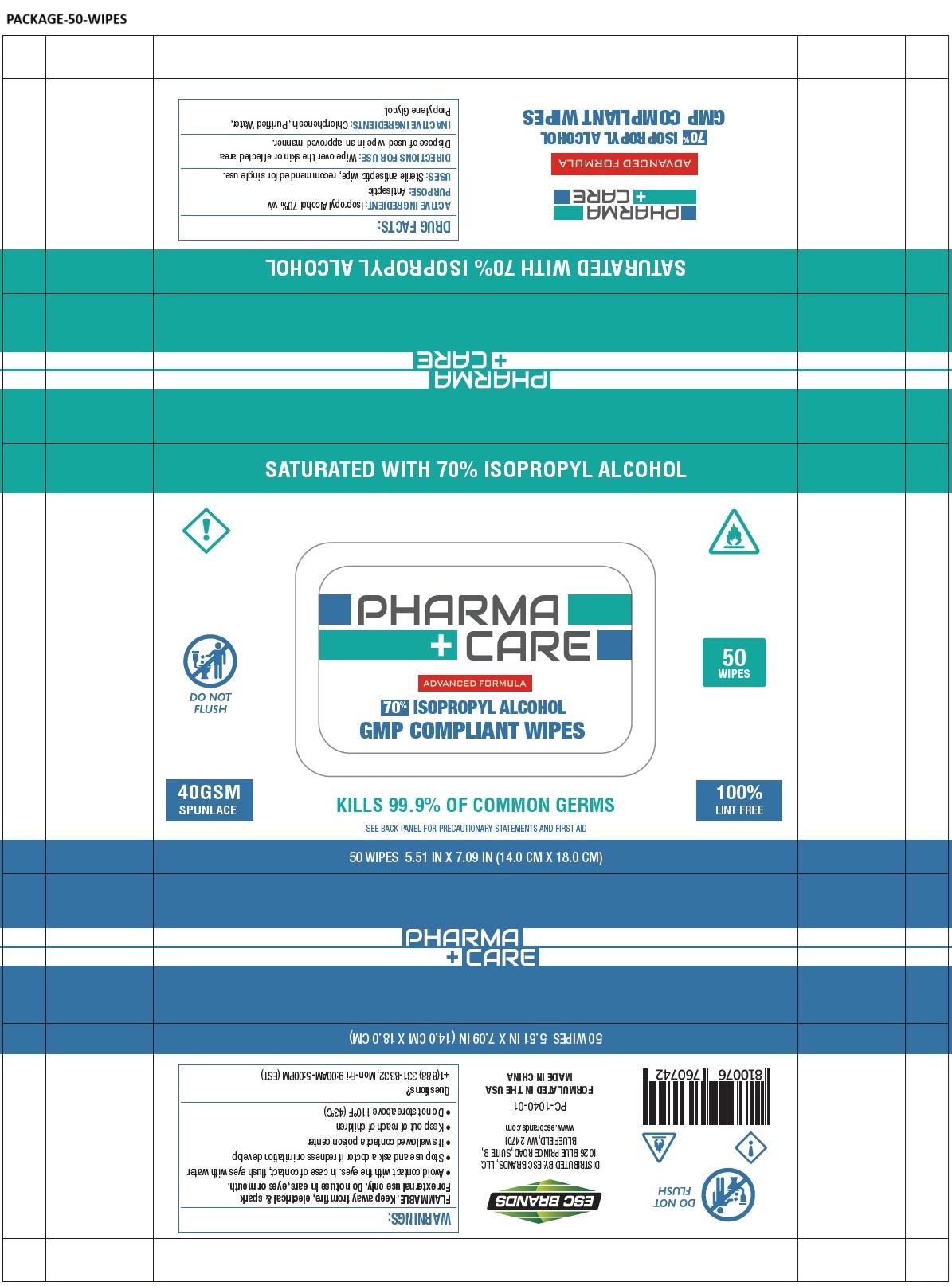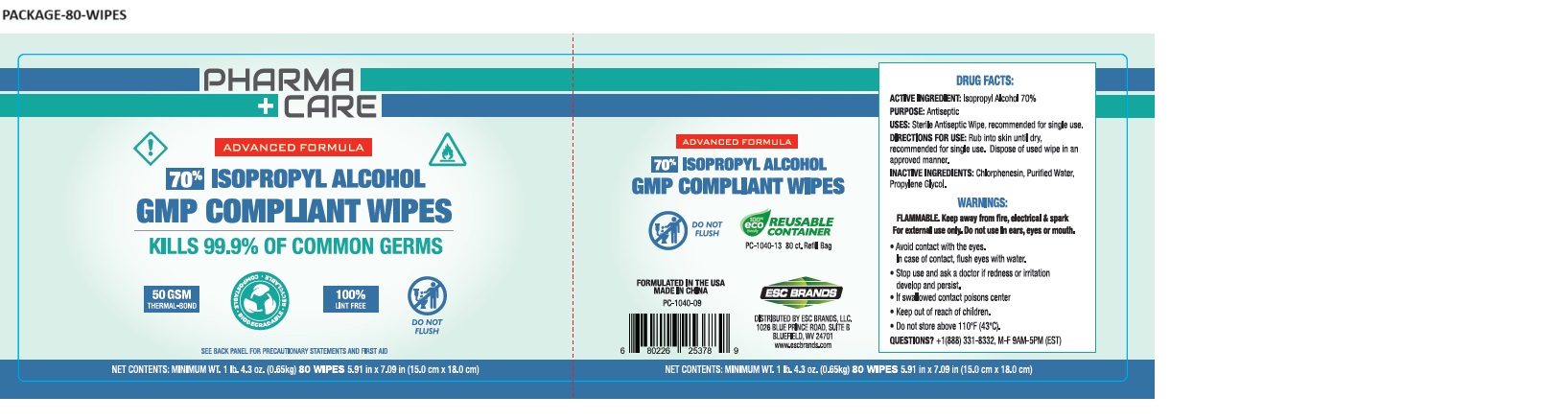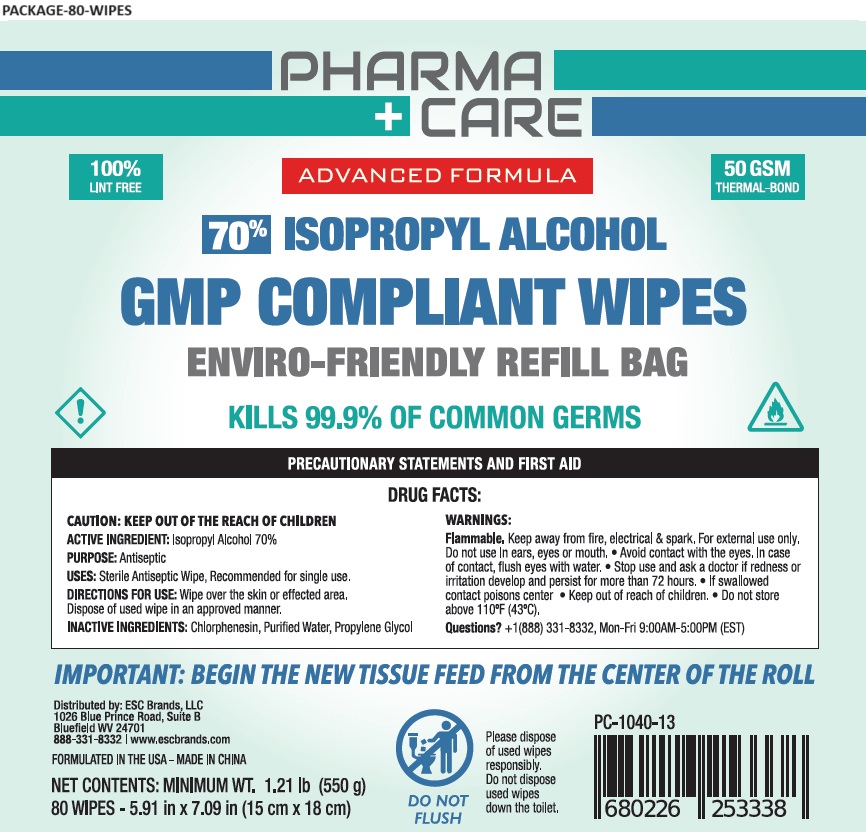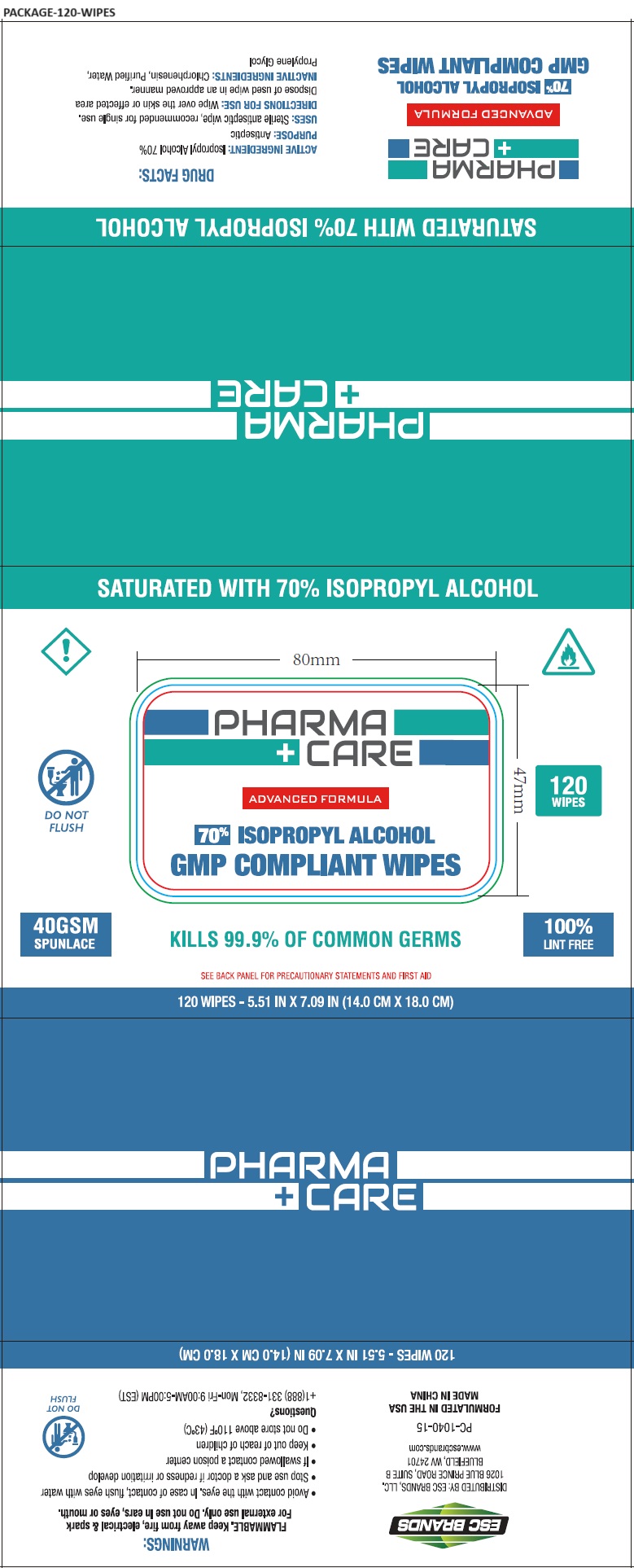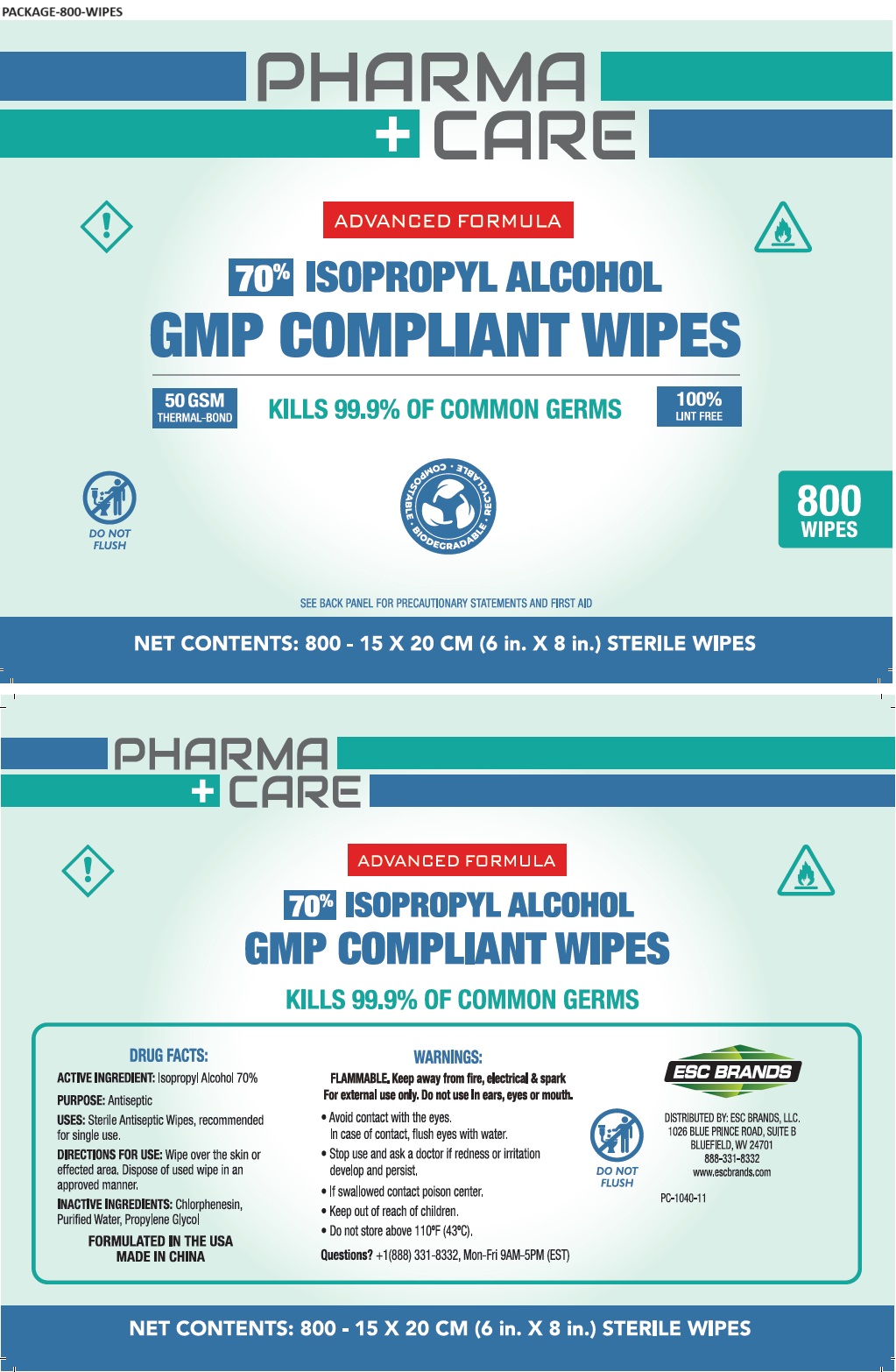 DRUG LABEL: Pharma care IPA Wipes
NDC: 71884-013 | Form: CLOTH
Manufacturer: Enviro Specialty Chemicals Inc
Category: otc | Type: HUMAN OTC DRUG LABEL
Date: 20250429

ACTIVE INGREDIENTS: ISOPROPYL ALCOHOL 70 mL/100 mL
INACTIVE INGREDIENTS: CHLORPHENESIN; WATER; PROPYLENE GLYCOL

Pharma care IPA Wipes

ACTIVE INGREDIENT:

Isopropyl Alcohol 70% v/v

PURPOSE:

Antiseptic

USES:

Sterile antiseptic wipe, recommended for single use.

DIRECTIONS FOR USE:

Wipe over the skin or effected area, recommended for single use, dispose of used wipe in an approved manner.

WARNINGS:

FLAMMABLE. Keep away from fire, electrical & spark

For external use only. Do not use In ears, eyes or mouth.

• Avoid contact with the eyes. In case of contact, flush eyes with water

• Stop use and ask a doctor if redness or irritation develop and persist

• If swallowed contact a poison center

• Do not store above 110°F(43°C)

• Keep out of reach of children.

INACTIVE INGREDIENTS:

Chlorphenesin, Purified Water, Propylene Glycol

QUESTIONS?

+1(888) 331 -8332, Mon-Fri 9:00AM-5:00PM (EST)

ADVANCED FORMULA

GMP COMPLIANT WIPES

KILLS 99.9% OF COMMON GERMS

40 GSM SPUNLACE

45 GSM SPUNLACE

50 GSM SPUNLACE

100% LINT FREE

SATURATED WITH 70% ISOPROPYL ALCOHOL

Single use pads in foil packages

Thicker and softer than other pads

2-ply design for efficient use and tearing resistance

Longer shelf life

DO NOT FLUSH

DISTRIBUTED BY: ESC BRANDS, LLC.
1026 BLUE PRINCE ROAD, SUITE B,
BLUEFIELD WV 24701

www.escbrands.com

FORMULATED IN THE USA

MADE IN CHINA